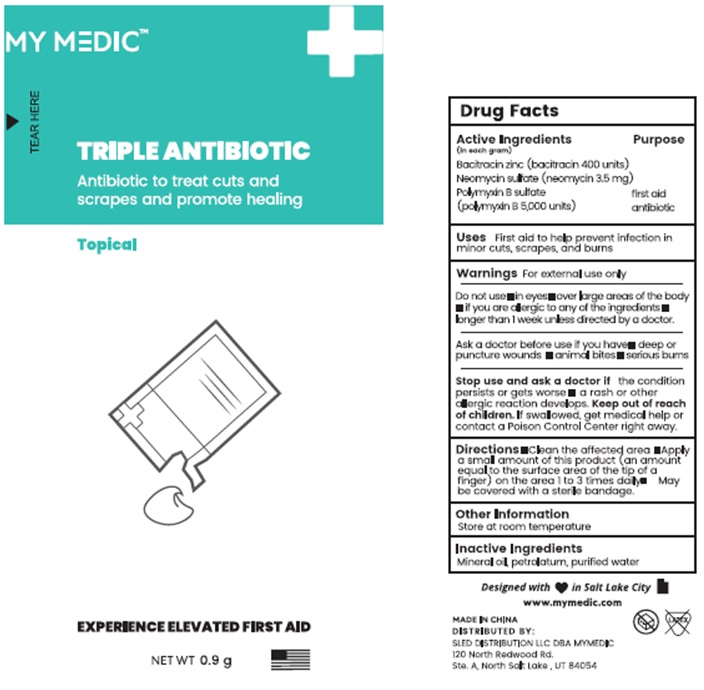 DRUG LABEL: Triple Antibiotic
NDC: 81417-003 | Form: OINTMENT
Manufacturer: Sled Distribution, LLC
Category: otc | Type: HUMAN OTC DRUG LABEL
Date: 20240115

ACTIVE INGREDIENTS: BACITRACIN ZINC 400 [USP'U]/1 g; NEOMYCIN SULFATE 0.0035 g/1 g; POLYMYXIN B SULFATE 5000 [USP'U]/1 g
INACTIVE INGREDIENTS: MINERAL OIL; PETROLATUM; WATER

81417-003 MY MEDIC TRIPLE ANTIBIOTIC

Active Ingredient

(in each gram)

Bacitracin Zinc (bacitracin 400 units)

Neoycin sulfate (neoycin 3.5 mg)

Polymyxin B sulfate

(polymyxin B 5,000 units)

Purpose

first aid antibiotic

Uses

First aid to help prevent infection in minor cuts, scrapes, and burns

Warning

For external use only.

Do not use

- in eyes
- over large areas of the body
- if you are allergic to any of the ingredients
- longer than 1 week unless directed by a doctor

Ask a doctor before use if you have

- deep or puncture wounds
- animal bites,
- serious burns

Stop use and ask a doctor if

- the condition persists or gets worse
- a rash or other allergic reaction develops

Keep out of reach of children. If swallowed, get medical help or contact a Poison Control Center right away.

Directions

Clean the affected area
Apply a small amount of this product (an amount equal to the surface area of the tip of a finger) on the area 1 to 3 times daily
May be covered with a sterile bandage

STORAGE AND HANDLING

Store at room temperature

Inactive ingredients

Mineral oil, Petrolatum, Purified water